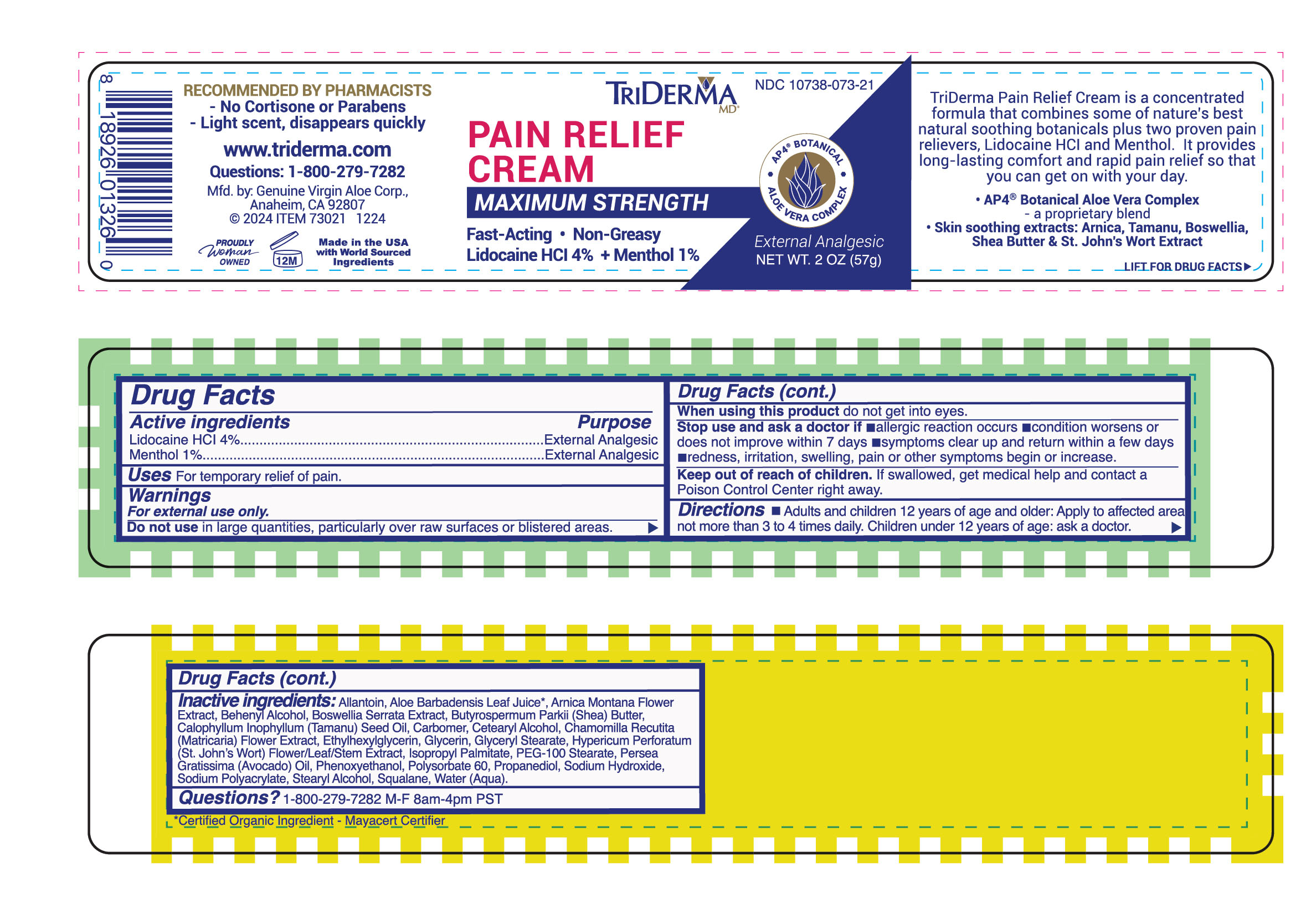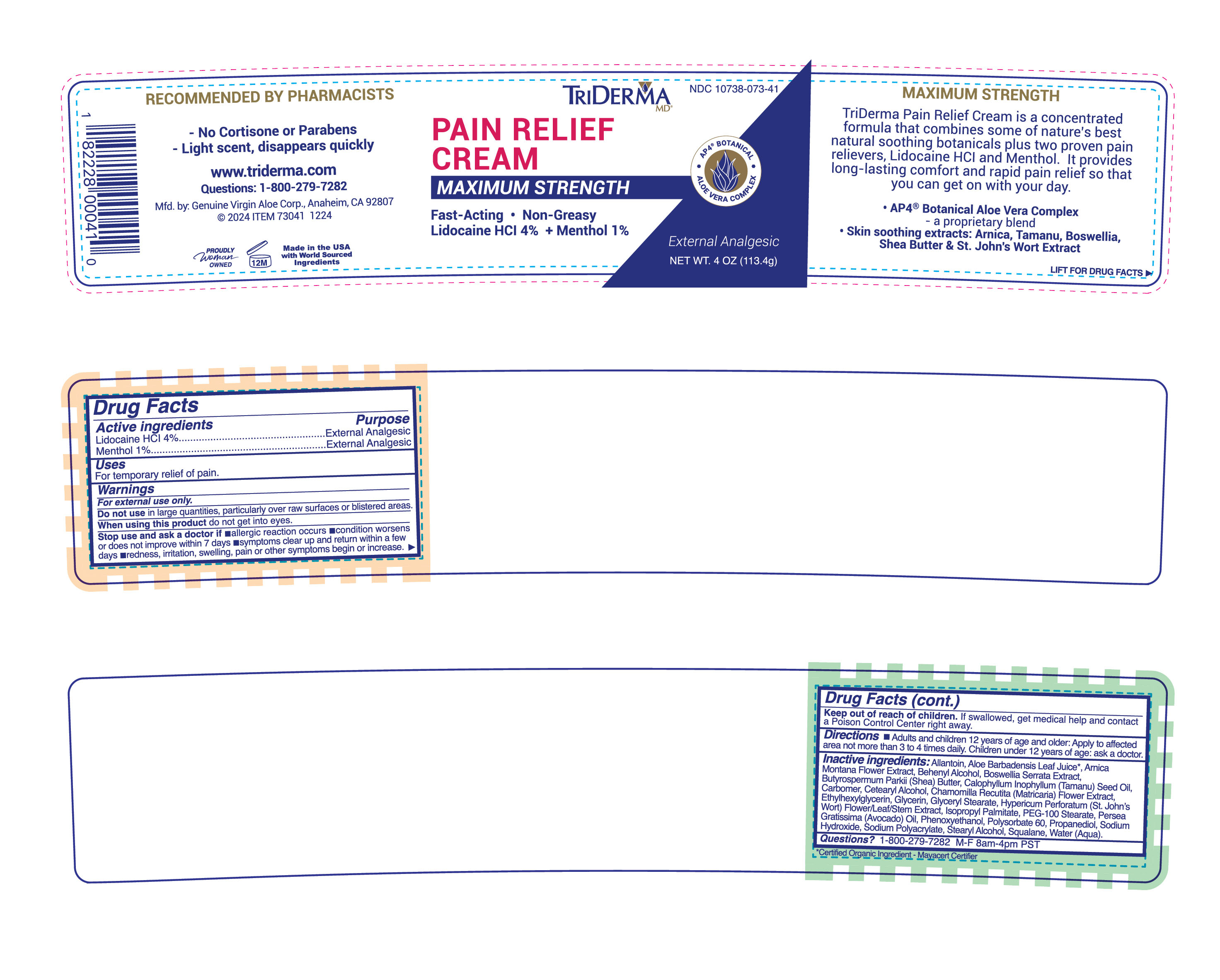 DRUG LABEL: TRIDERMA PAIN RELIEF
NDC: 10738-073 | Form: CREAM
Manufacturer: Genuine Virgin Aloe Corporation
Category: otc | Type: HUMAN OTC DRUG LABEL
Date: 20260127

ACTIVE INGREDIENTS: LIDOCAINE HYDROCHLORIDE 4 g/100 g; MENTHOL, UNSPECIFIED FORM 1 g/100 g
INACTIVE INGREDIENTS: SQUALANE; SODIUM HYDROXIDE; SODIUM POLYACRYLATE (8000 MW); PROPANEDIOL; WATER; MEDIUM-CHAIN TRIGLYCERIDES; ISOPROPYL PALMITATE; GLYCERIN; STEARYL ALCOHOL; SHEA BUTTER; CARBOMER INTERPOLYMER TYPE A (ALLYL SUCROSE CROSSLINKED); GLYCERYL MONOSTEARATE; PEG-100 STEARATE; ALLANTOIN; CETOSTEARYL ALCOHOL; AVOCADO OIL; TAMANU OIL; POLYSORBATE 60; ST. JOHN'S WORT; ALOE VERA LEAF; ARNICA MONTANA FLOWER; CHAMOMILE; PHENOXYETHANOL; ETHYLHEXYLGLYCERIN; BEHENYL ALCOHOL

TRIDERMA PAIN RELIEF CREAM

Active ingredients

Lidocaine HCl 4.0%

Menthol 1.0%

Purpose

Topical Analgesic

INDICATIONS AND USAGE

Uses For temporary relief of pain

Warnings For external use only.

Ask a doctor before use if you have a heart condition.

Do not use •if you are allergic to any other type of numbing medicine •in large quantities, particularly over raw surfaces or blistered areas •on infections •on deep puncture wounds •if pregnant or breastfeeding.

When using this product •do not use over large skin areas •do not apply heat, bandages or plastic wrap to treated areas •do not use in or near the eyes •wash hands immediately after using.

Stop use and ask a doctor if •allergic reaction occurs •condition worsens or does not improve within 7 days •symptoms clear up and return within a few days •redness, irritation, swelling, pain or other symptoms begin or increase.

Keep out of reach of children. If swallowed get medical help or contact a Poison Control Center right away.

DOSAGE AND ADMINISTRATION

Directions • apply generously up to 3 to 4 times daily. For use on adults and children 12 years and older. Children under 12 - ask a doctor.

INACTIVE INGREDIENT

Inactive ingredients:Allantoin, Aloe Barbadensis Leaf Juice*, Arnica Montana Flower Extract, Behenyl Alcohol, Boswellia Serrata Extract, Butyrospermum Parkii (Shea) Butter, Calophyllum Inophyllum (Tamanu) Seed Oil, Carbomer, Cetearyl Alcohol, Chamomilla Recutita (Matricaria) Flower Extract, Ethylhexylglycerin, Glycerin, Glyceryl Stearate, Hypericum Perforatum (St. John's Wort) Flower/Leaf/Stem Extract, Isopropyl Palmitate, PEG-100 Stearate, Persea Gratissima (Avocado) Oil, Phenoxyethanol, Polysorbate 60, Propanediol, Sodium Hydroxide, Sodium Polyacrylate, Stearyl Alcohol, Squalane, Water (Aqua) .

*Certified Organic Ingredient - Mayacert Certifier

QUESTIONS

Questions? 1-800-279-7282 M-F 8am-4pm PST

No Burning · Non-Greasy

Temporarily relieves minor aches & pains of muscles & joints from arthritis, simple backaches, strains, sprains & bruises

AP4 BOTANICAL

ALOE VERA COMPLEX

With Lidocaine HCl & Menthol

This specialized formula combines two proven maximum strength pain relievers, Lidocaine HCl and Menthol for minor relief of all types of aches and pains. It’s ideal for Arthritis, simple backaches, muscle strains, bruises, minor cuts, scrapes, skin irritations and even insect bites.

Contains No Cortisone or Parabens

visit www.triderma.com

Mfd. by: Genuine Virgin Aloe Corp., Anaheim, CA 92807

Pain Relief Cream is a unique formula that helps provide long-lasting comfort and fast pain relief.

It combines the best of nature’s healing botanicals and science to help relieve pain, so that you can get on with your day.

· AP4® Aloe Vera Complex is a proprietary botanical blend made with Certified Organic Aloe Vera*.

· St. John’s Wort, Arnica & Boswellia

· Contains a touch of Menthol for extra pain relief - light scent, disappears quickly.